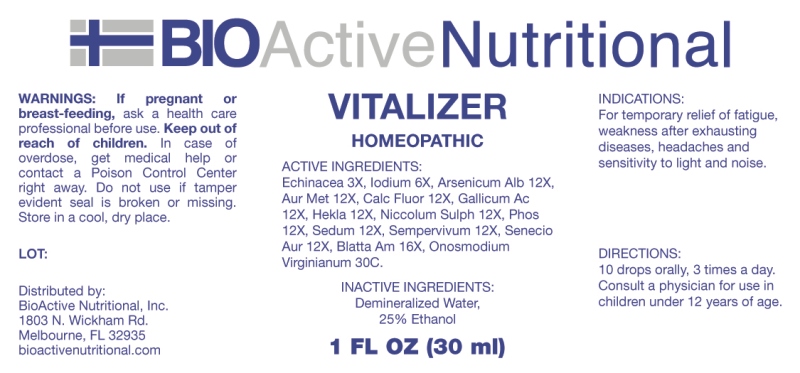 DRUG LABEL: Vitalizer
NDC: 43857-0629 | Form: LIQUID
Manufacturer: BioActive Nutritional, Inc.
Category: homeopathic | Type: HUMAN OTC DRUG LABEL
Date: 20230406

ACTIVE INGREDIENTS: ECHINACEA ANGUSTIFOLIA WHOLE 3 [hp_X]/1 mL; IODINE 6 [hp_X]/1 mL; ARSENIC TRIOXIDE 12 [hp_X]/1 mL; GOLD 12 [hp_X]/1 mL; CALCIUM FLUORIDE 12 [hp_X]/1 mL; GALLIC ACID MONOHYDRATE 12 [hp_X]/1 mL; HEKLA LAVA 12 [hp_X]/1 mL; NICKEL SULFATE HEXAHYDRATE 12 [hp_X]/1 mL; PHOSPHORUS 12 [hp_X]/1 mL; SEDUM ACRE WHOLE 12 [hp_X]/1 mL; SEMPERVIVUM TECTORUM LEAF 12 [hp_X]/1 mL; PACKERA AUREA WHOLE 12 [hp_X]/1 mL; PERIPLANETA AMERICANA 16 [hp_X]/1 mL; ONOSMODIUM VIRGINIANUM 30 [hp_C]/1 mL
INACTIVE INGREDIENTS: WATER; ALCOHOL

DRUG FACTS:

ACTIVE INGREDIENTS:

Echinacea 3X, Iodium 6X, Arsenicum Album 12X, Aurum Metallicum 12X, Calcarea Fluorica 12X, Gallicum Acidum 12X, Hekla Lava 12X, Niccolum Sulphuricum 12X, Phosphorus 12X, Sedum Acre 12X, Sempervivum Tectorum 12X, Senecio Aureus 12X, Blatta Americana 16X, Onosmodium Virginianum 30C.

PURPOSE:

For temporary relief of fatigue, weakness after exhausting diseases, headaches and sensitivity to light and noise.

WARNINGS:

If pregnant or breast-feeding, ask a health care professional before use.

Keep out of reach of children. In case of overdose, get medical help or contact a Poison Control Center right away.

Do not use if tamper evident seal is broken or missing.

Store in cool, dry place.

KEEP OUT OF REACH OF CHILDREN:

In case of overdose, get medical help or contact a Poison Control Center right away.

DIRECTIONS:

10 drops orally, 3 times a day. Consult a physician for use in children under 12 years of age.

INDICATIONS:

For temporary relief of fatigue, weakness after exhausting diseases, headaches and sensitivity to light and noise.

INACTIVE INGREDIENTS:

Demineralized Water, 25% Ethanol

QUESTIONS:

Distributed by:
BioActive Nutritional, Inc.
1803 N. Wickham Rd.
Melbourne, FL 32935
bioactivenutritional.com

PACKAGE LABEL DISPLAY:

BIOActive Nutritional

VITALIZER

HOMEOPATHIC

1 FL OZ (30 ml)